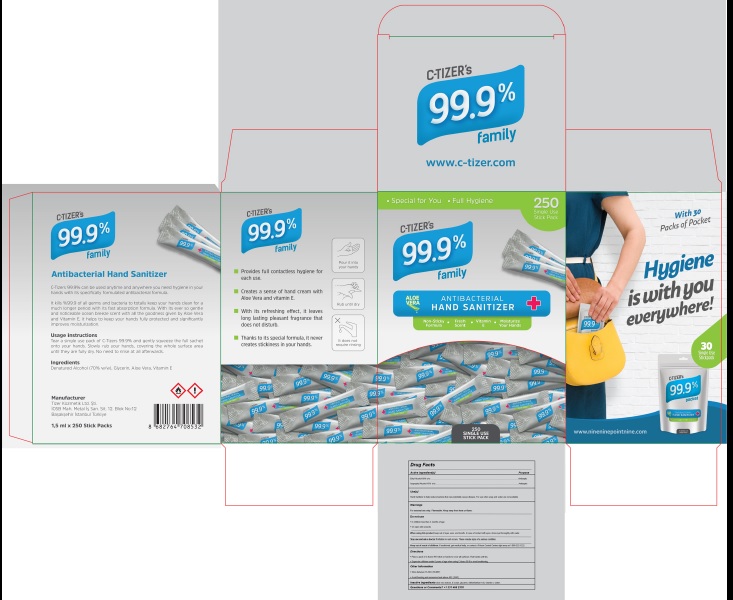 DRUG LABEL: C-tizers 99.9
NDC: 80637-001 | Form: GEL
Manufacturer: TIZER KOZMETIK LIMITED SIRKETI
Category: otc | Type: HUMAN OTC DRUG LABEL
Date: 20201207

ACTIVE INGREDIENTS: ALCOHOL 60 mL/100 mL; ISOPROPYL ALCOHOL 10 mL/100 mL
INACTIVE INGREDIENTS: .ALPHA.-TOCOPHEROL; GLYCERIN; ALOE VERA LEAF; TROLAMINE; CARBOMER HOMOPOLYMER TYPE C (ALLYL PENTAERYTHRITOL CROSSLINKED); FD&C BLUE NO. 1; WATER

Active Ingredient Purpose

Ethyl Alcohol 60% v/v........................ Antiseptic

Isopropyl Alcohol 10% v/v.................. Antiseptic

Uses

Antibacterial Hand Sanitizer.

Warnings

Flammable, Keep away from eyes.

Directions

Tear a single use pack of C-Tizers 99.9% and gently squeeze the full sachet onto your hands. Slowly rub your hands, covering the whole surface area until they are fully dry. No need to rinse at all afterwards.

Inactive ingredients

2,2,2-Nitrilotri(ethan-1-ol), Glycerin, Aloe vera extract, (2R)-2,5,7,8-tetramethyl-2-[(4R,8R)-4,8,12-trimethyltridecyl]-3,4-dihydro-2H-1-benzopyran-6-ol, CarboxyvinylPolymer, B.OCEAN 345276, C.I.:42090, Water.